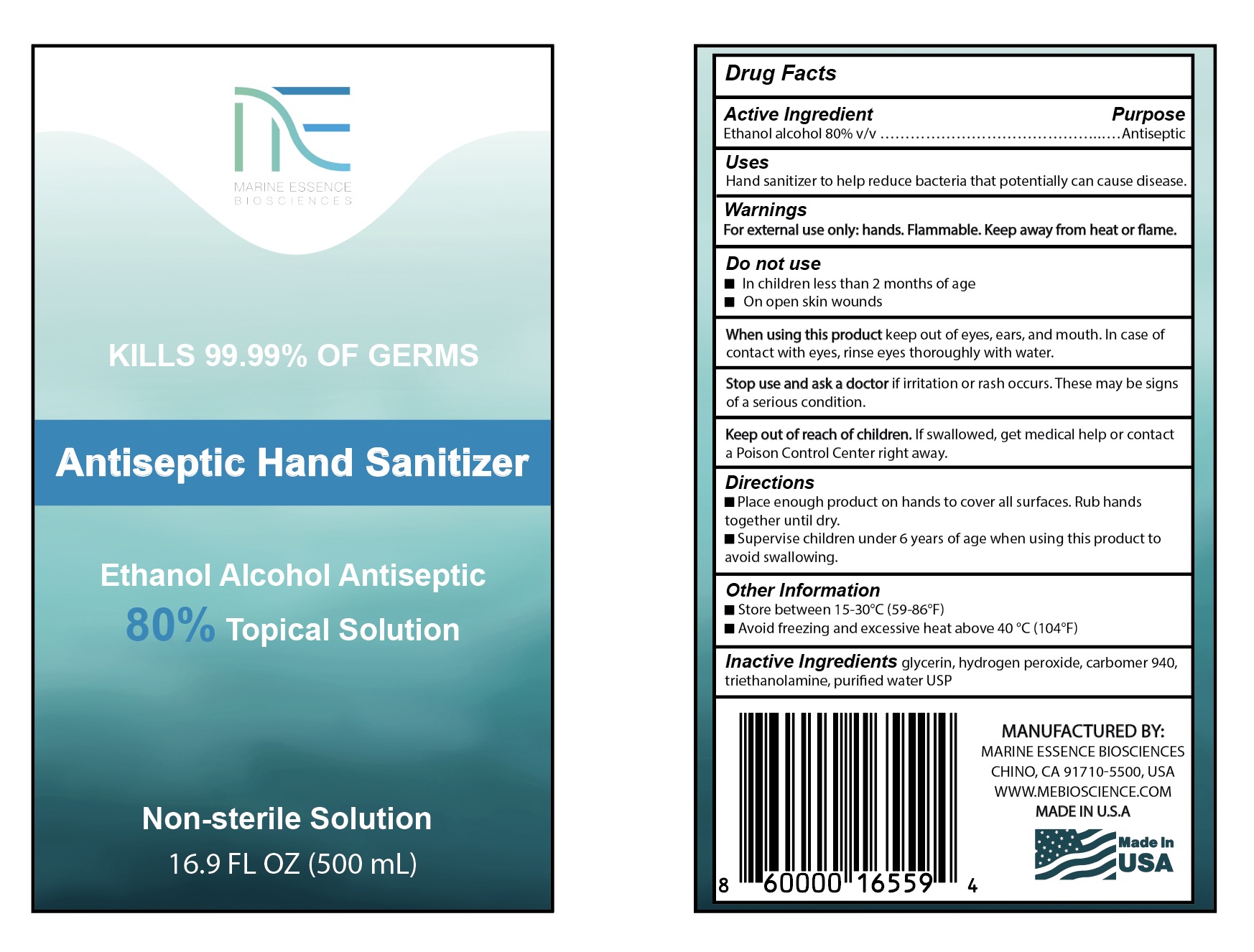 DRUG LABEL: Ethyl Alcohol
NDC: 73764-002 | Form: GEL
Manufacturer: Marine Essence Biosciences Corporation of USA
Category: otc | Type: HUMAN OTC DRUG LABEL
Date: 20200603

ACTIVE INGREDIENTS: ALCOHOL 80 mL/100 mL
INACTIVE INGREDIENTS: HYDROGEN PEROXIDE; WATER; GLYCERIN; TROLAMINE; CARBOMER 940

Ethyl Alcohol Hand Sanitizer

ACTIVE INGREDIENT

Ethanol alcohol 80% v/v ……………………………………..………………………………………………………………………...Antiseptic

PURPOSE

Hand sanitizer to help reduce bacteria that potentially can cause disease.

INACTIVE INGREDIENT

glycerin, hydrogen peroxide, carbomer 940, triethanolamine, purified water USP

DOSAGE AND ADMINISTRATION

Topical - Administration to a particular spot on the outer surface of the body. The E2B term TRANSMAMMARY is a subset of the term TOPICAL

WHEN USING

For external use only. Flammable. Keep away from heat or flame

When using this product keep out of eyes, ears, and mouth. In case of contact with eyes, rinse eyes thoroughly with water.

DO NOT USE

In children less than 2 months of age

On open skin wounds

Stop use and ask a doctor if irritation or rash occurs. These may be signs of a serious condition.

Keep out of reach of children. If swallowed, get medical help or contact a Poison Control Center right away.

INSTRUCTIONS FOR USE

Place enough product on hands to cover all surfaces. Rub hands together until dry.

Supervise children under 6 years of age when using this product to avoid swallowing.

Other Information

Store between 15-30C (59-86F)

Avoid freezing and excessive heat above 40C (104F)

DOSAGE FORMS AND STRENGTHS

Gel form

Warnings for external use only-hands

INDICATIONS AND USAGE

To help reduce bacteria on the hands that can potentially cause disease.